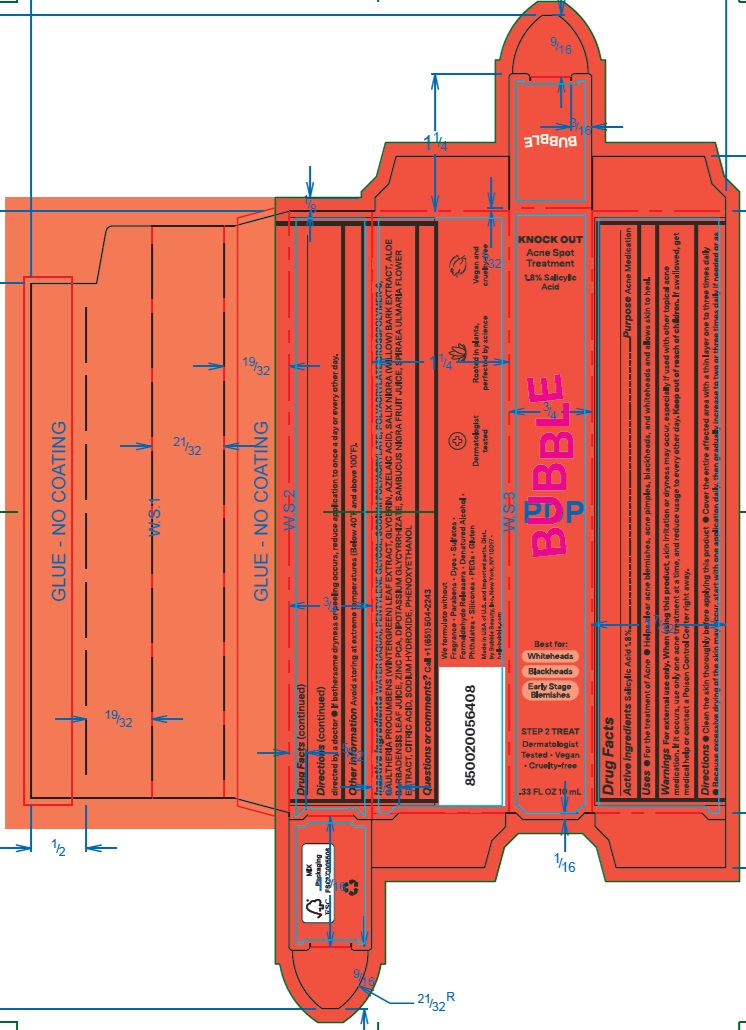 DRUG LABEL: Bubble Knock Out Acne Spot Treatment
NDC: 83509-002 | Form: EMULSION
Manufacturer: BUBBLE BEAUTY
Category: otc | Type: HUMAN OTC DRUG LABEL
Date: 20240506

ACTIVE INGREDIENTS: SALICYLIC ACID 18 mg/1 mL
INACTIVE INGREDIENTS: PENTYLENE GLYCOL; SODIUM POLYACRYLATE (2500000 MW); AMMONIUM ACRYLOYLDIMETHYLTAURATE, DIMETHYLACRYLAMIDE, LAURYL METHACRYLATE AND LAURETH-4 METHACRYLATE COPOLYMER, TRIMETHYLOLPROPANE TRIACRYLATE CROSSLINKED (45000 MPA.S); SALIX NIGRA BARK; GAULTHERIA PROCUMBENS LEAF; AZELAIC ACID; FILIPENDULA ULMARIA FLOWER; ALOE VERA LEAF; ZINC PIDOLATE; EUROPEAN ELDERBERRY JUICE; CITRIC ACID MONOHYDRATE; SODIUM HYDROXIDE; WATER; PHENOXYETHANOL; GLYCERIN; GLYCYRRHIZINATE DIPOTASSIUM

Bubble Knock Out Acne Spot Treatment

Active ingredients

Salicylic Acid 1.8%

Purpose

Acne Medication

Uses

- For the treatment of acne
- Helps clear acne blemishes, acne pimples, blackheads, and whiteheads and allows skin to heal.

Warnings

For external use only.

When using this product

skin irritation or dryness may occur, especiallly if used with other topical acne medication. If it occurs, use only one acne treatment at a time, and reduce usage to every other day.

Keep out of reach of children.

If swallowed, get medical help or contact a Poison Control Center right away.

Directions

- Clean the skin thoroughly before applying this product. Cover the entire affected area with a thin layer one to three times daily.
- Because excessive drying of the skin may occur, start with one application daily, then gradually increase to two or three times daily if needed or as directed by a doctor.
- If bothersome dryness or peeling occurs, reduce application to once a day or every other day.

Other information

- Avoid storing at extreme temperatures (Below 40F and above 100F).

Inactive ingredients

WATER (AQUA), PENTYLENE GLYCOL, SODIUM POLYACRYLATE, POLYACRYLATE CROSSPOLYMER-6, GAULTHERIA PROCUMBENS (WINTERGREEN) LEAF EXTRACT, GLYCERIN, AZELAIC ACID, SALIX NIGRA (WILLOW) BARK EXTRACT, ALOE BARBADENSIS LEAF JUICE, ZINC PCA, DIPOTASSIUM GLYCYRRHIZATE, SAMBUCUS NIGRA FRUIT JUICE, SPIRAEA ULMARIA FLOWER EXTRACT, CITRIC ACID, SODIUM HYDROXIDE, PHENOXYETHANOL

Questions or comments?

Call +1 (651) 504-2243